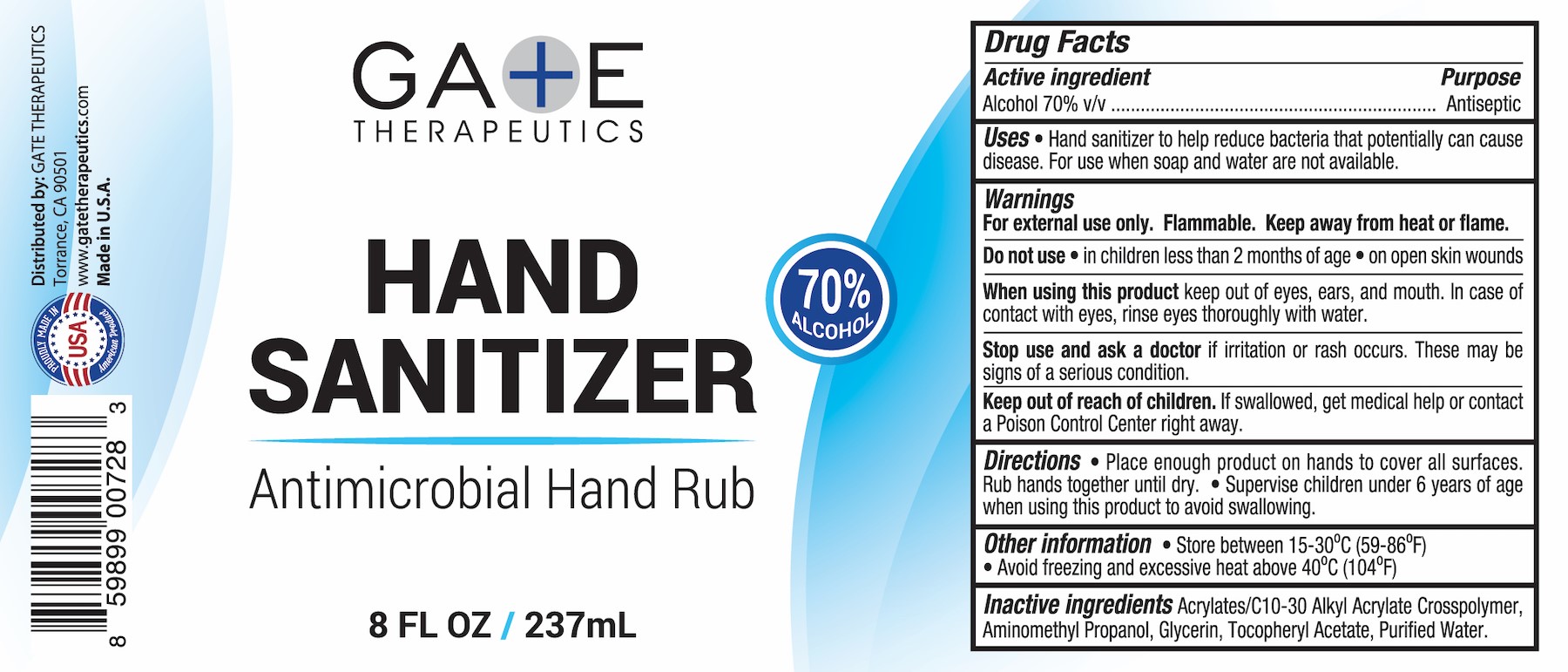 DRUG LABEL: Hand Sanitizer Antimicrobial Hand Rub
NDC: 72274-003 | Form: SOLUTION
Manufacturer: GATE THERAPEUTICS
Category: otc | Type: HUMAN OTC DRUG LABEL
Date: 20211110

ACTIVE INGREDIENTS: ALCOHOL 70 mL/100 mL
INACTIVE INGREDIENTS: .ALPHA.-TOCOPHEROL ACETATE; GLYCERIN; CARBOMER INTERPOLYMER TYPE A (ALLYL SUCROSE CROSSLINKED); WATER; AMINOMETHYLPROPANOL

Hand Sanitizer Antimicrobial Hand Rub

Active Ingredient(s)

Alcohol 70% v/v. Purpose: Antiseptic

Purpose

Antiseptic

Use

Hand Sanitizer to help reduce bacteria that potentially can cause disease. For use when soap and water are not available.

Warnings

For external use only. Flammable. Keep away from heat or flame

Do not use

- in children less than 2 months of age
- on open skin wounds

When using this product keep out of eyes, ears, and mouth. In case of contact with eyes, rinse eyes thoroughly with water.
Stop use and ask a doctor if irritation or rash occurs. These may be signs of a serious condition.
Keep out of reach of children. If swallowed, get medical help or contact a Poison Control Center right away.

Stop use and ask a doctor if irritation or rash occurs. These may be signs of a serious condition.

Keep out of reach of children. If swallowed, get medical help or contact a Poison Control Center right away.

Directions

- Place enough product on hands to cover all surfaces. Rub hands together until dry.
- Supervise children under 6 years of age when using this product to avoid swallowing.

Other information

- Store between 15-30C (59-86F)
- Avoid freezing and excessive heat above 40C (104F)

Inactive ingredients

Acrylates/C10-30 Alkyl Acrylate Crosspolymer, Aminomethyl Propanol, Glycerin, Tocopheryl Acetate, Water

Package Label - Principal Display Panel

Gaate Therapeutics

Hand Sanitizer

Antimicrobial Hand Rub

8 FL OZ / 237mL